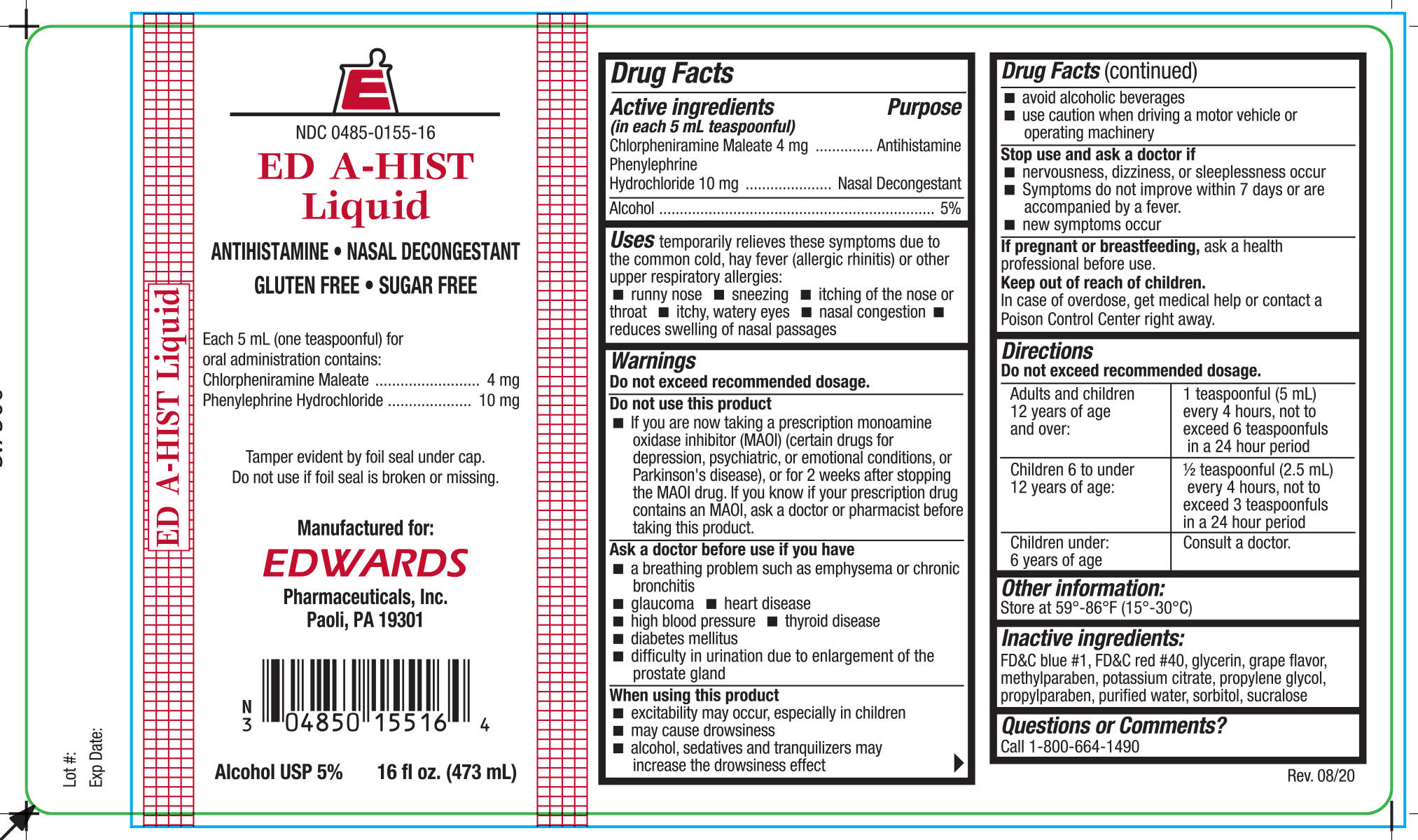 DRUG LABEL: ED A-HIST
NDC: 0485-0155 | Form: LIQUID
Manufacturer: Edwards Pharmaceuticals, Inc.
Category: otc | Type: HUMAN OTC DRUG LABEL
Date: 20251028

ACTIVE INGREDIENTS: CHLORPHENIRAMINE MALEATE 4 mg/5 mL; PHENYLEPHRINE HYDROCHLORIDE 10 mg/5 mL
INACTIVE INGREDIENTS: GLYCERIN; WATER; SODIUM CITRATE; SACCHARIN SODIUM; SORBITOL; PROPYLENE GLYCOL; ALCOHOL

ED A-HIST LIQUID

Drug Facts

Active ingredients (in each 5 mL teaspoonful)

Chlorpheniramine Maleate 4mg

Phenylephrine Hydrochloride 10 mg

Alcohol.............................................5%

Purpose

Antihistamine.........................Nasal Decongestant

Uses

temporarily relieves runny nose and nasal congestion due to the common cold, hay fever or other upper respiratory allergies allergic rhinitis), relieves sneezing, itching of the nose or throat, itchy watery eyes, and reduces swelling of the nasal passages.

Warnings: Do not exceed recommended dosage.

Do not use this product

- if you are now taking prescription monaimine oxidase inhibitor (MAOI) (certain drugs for depression, psychiatric, or emotional conditions, or Parkinson's disease), or for 2 weeks after stopping the MAOI drug. If you know if your prescription drug contains an MAOI, ask a doctor or pharmacist before taking this product.

Do not take this product, unless directed by a doctor before use if you have

- A breathing problem such as emphysema or chronic bronchitis
- Glaucoma, heart disease, diabetes, high blood pressure or thyroid disease
- Difficulty in urination due to enlargement of the prostate gland

Ask a doctor or pharmacist before use if you are

taking sedatives or tranquilizers.

When using the product

- May cause drowsiness
- Avoid alcoholic beverages
- Alcohol, sedatives, and tranquilizers may increase drowsiness
- Be careful when driving a motor vehicle or operating machinery
- Excitability may occur, especially in children.

Stop use and ask a doctor if

- Nervousness, dizziness, or sleeplessness occurs
- Symptoms do not improve within 7 days or are accompanied by a fever.

If pregnant or breast-feeding,

ask a health professional before use.

Keep out of reach of children.

In case of overdose, get medical help or contact a Poison Control Center right away.

Directions

Do not exceed recommended dosage.

Adults and children 12 years of age and over: | 1 teaspoonful (5 mL) every 4 hours, not to exceed 6 teaspoonfuls in a 24 hour period
Children 6 to under 12 years of age: | 1/2 teaspoonful (5 mL) every 4 hours, not to exceed 6 teaspoonfuls in a 24 hour period
Children under 6 years of age: | Consult a Doctor

A special measuring device should be used to give an accurate dose of this product to children under 12 years of age. Giving a higher dose than recommended by a doctor could result in serious side effects for your child.

Other information:

Store at 59° - 86°F (15° - 30°C)

Inactive ingredients:

FD and C Blue #1, Grape Flavor, Glycerin, Propylene Glycol, Purified Water, Sodium Citrate, Sodium Saccharin, Sorbitol, and FD and C Red #40.

Questions or comments?

Call 1-800-543-9560

Iss. 12/10

Product Packaging

The packaging below represents the labeling currently used:

Principal display panel and side panel for 473 mL label:

NDC 0485-0155-16
ED A-HIST LIQUID
ANTIHISTAMINE / DECONGESTANT
Each 5 mL (one teaspoonful) for oral administration contains:
Chlorpheniramine Maleate..............................4 mg
Phenyleprhing Hydrochloride.........................10 mg
Alcohol USP.....................................................5%

GLUTEN FREE / SUGAR FREE

DO NOT USE IF FOIL SEAL UNDER CAP IS BROKEN OR MISSING

Manufactured for:
EDWARDS Pharmaceuticals, Inc.
Paoli, PA 19301

Net Contents: 1 pint (473 mL)

Tamper evident by foil seal under cap. Do not use if foil seal is broken or missing.

dispense in a tight, light-resistant container with a child-resistant closure.

This bottle is not to be dispensed to consumer.